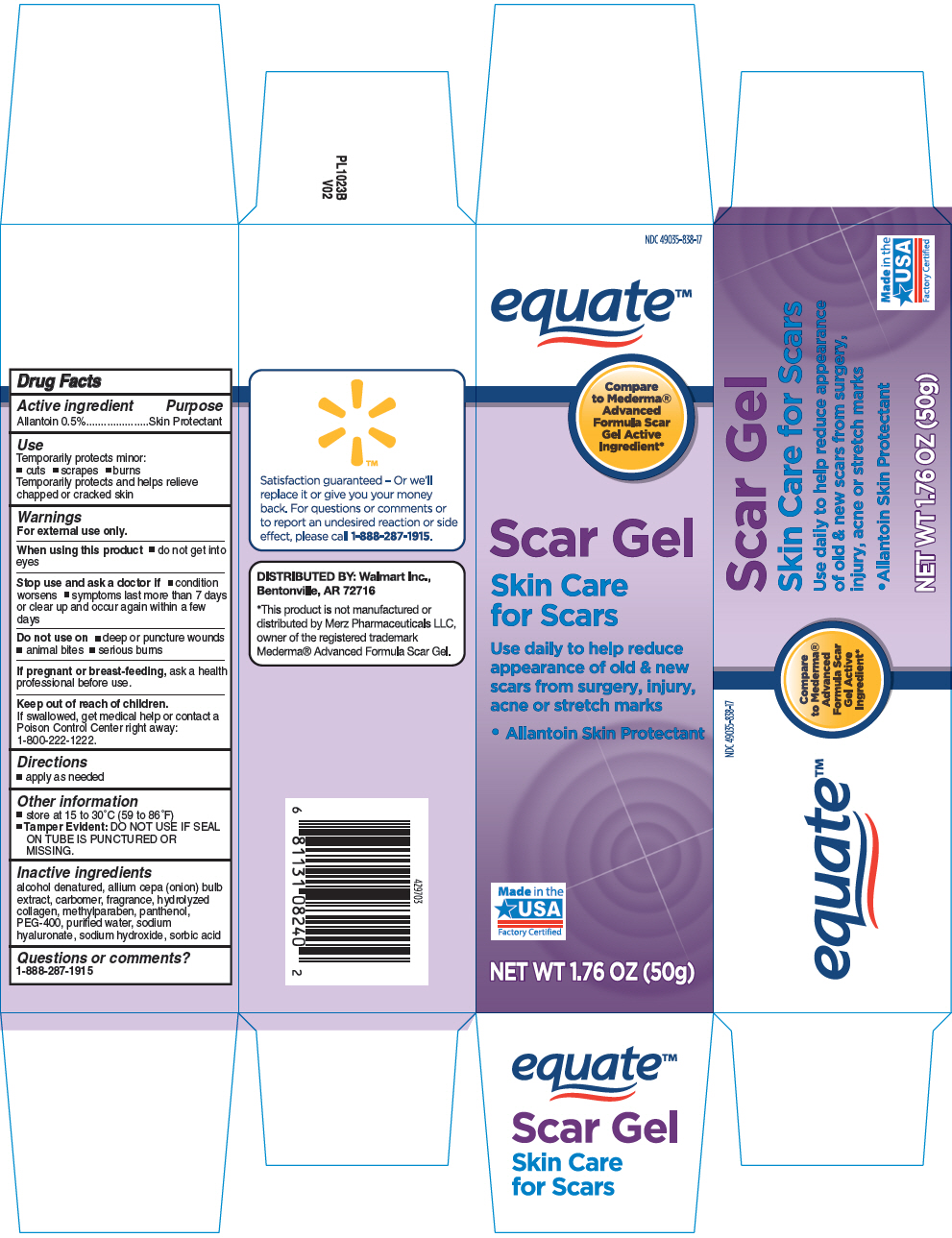 DRUG LABEL: Equate Scar
NDC: 49035-838 | Form: CREAM
Manufacturer: WalMart
Category: otc | Type: HUMAN OTC DRUG LABEL
Date: 20260129

ACTIVE INGREDIENTS: ALLANTOIN 0.005 mg/1 g
INACTIVE INGREDIENTS: CARBOMER HOMOPOLYMER TYPE C (ALLYL PENTAERYTHRITOL CROSSLINKED); HUMAN TYPE III COLLAGEN; METHYLPARABEN; ONION; PANTHENOL; POLYETHYLENE GLYCOL 400; WATER; ALCOHOL; HYALURONATE SODIUM; SODIUM HYDROXIDE; SORBIC ACID

Equate™ Scar Gel
Topical

Drug Facts

Active ingredient

Allantoin 0.5%

Purpose

Skin Protectant

Use

Temporarily protects minor:

- cuts
- scrapes
- burns

Temporarily protects and helps relieve chapped or cracked skin

Warnings

For external use only.

Do not use on

- deep or puncture wounds
- animal bites
- serious burns

When using this product

- do not get into eyes

Stop use and ask a doctor if

- condition worsens
- symptoms last more than 7 days or clear up and occur again within a few days

PREGNANCY OR BREAST FEEDING

If pregnant or breast-feeding, ask a health professional before use.

Keep out of reach of children.

If swallowed, get medical help or contact a Poison Control Center right away: 800-222-1222.

Directions

- apply as needed

Other information

- store at 15 to 30°C (59 to 86°F)
- Tamper Evident: DO NOT USE IF SEAL ON TUBE IS PUNCTURED OR MISSING.

Inactive ingredients

alcohol denatured, allium cepa (onion) bulb extract, carbomer, fragrance, hydrolized collagen, methylparaben, panthenol, PEG-8, purified water, sodium hyaluronate, sodium hydroxide, sorbic acid

Questions or comments?

1-888-287-1915

DISTRIBUTED BY: Wal-Mart Stores, Inc.,
Bentonville, AR 72716

PRINCIPAL DISPLAY PANEL - 50 g Tube Carton

NDC 49035-838-17

equate™

Compare
to Mederma®
Advanced
Formula Scar
Gel Active
Ingredient*

Scar Gel

Skin Care
for Scars

Use daily to help reduce
appearance of old & new
scars from surgery, injury,
acne or stretch marks

- Allantoin Skin Protectant

Made in the
USA
Factory Certified

NET WT 1.76 OZ (50g)